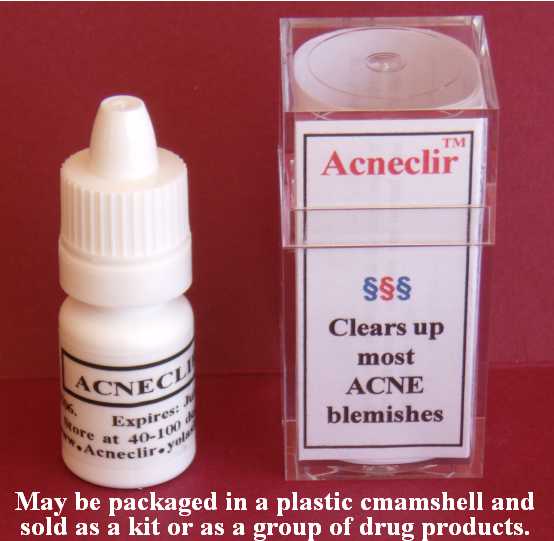 DRUG LABEL: Acneclir
NDC: 43074-110 | Form: LOTION
Manufacturer: Phillips Company
Category: otc | Type: HUMAN OTC DRUG LABEL
Date: 20100823

ACTIVE INGREDIENTS: SALICYLIC ACID 0.02 mL/1 mL
INACTIVE INGREDIENTS: dimethyl sulfoxide; ascorbic acid; dipropylene glycol; water; sorbic acid; magnesium stearate; stearic acid

DRUG FACTS

DRUG FACTS

Active Ingredient Purpose
Salicylic acid (2%) Acne medication
______________________________________
Uses
n Acne medication lotion. For the treatment of acne. Clears up most acne blemishes and allows skin to heal.
______________________________________
Warnings
n For external use only
n When using this product, skin irritation and dryness is more likely to occur if you use another topical acne medication at the same time. If irritation occurs, only use one topical acne medication at a time.
n Keep away from children
n Avoid contact with eyes
n May be harmful if swallowed or inhaled
______________________________________
Ask a physician
n If symptoms last for more than 7 days or clear up and recur within a few days.
n If the conditions do not improve.
n Before use on children under 2 years.
n Before use if you are allergic to any ingredients listed on this label.
______________________________________
Directions
n Clean the skin thoroughly before applying this product.
n Apply product sparingly to one or two small affected areas during the first 3 days. If no discomfort occurs, follow the directions stated below.
n Each morning, cover the entire affected area with a thin layer of this product.
n Apply this product by rubbing it in. If any liquid remains on the skin (after a 20-second rub-in), you have applied too much product.
______________________________________
Other information
Store at 40 to 100 degrees F. Net contents: 3 mL. This product contains no alcohol; no animal products.
______________________________________
Inactive ingredients
Water, dimethyl sulfoxide, dipropylene glycol, ascorbic acid, sorbic acid, magnesium stearate, stearic acid.
______________________________________
Questions and Side effects
Use of this product results in no known side effects when used according to directions. Phillips Company, 311 Chickasaw Street, Millerton, OK USA 74750; Tel. 580-746-2430
Email address: hp@valliant.net

ACTIVE INGREDIENTS

Active Ingredient Purpose
Salicylic acid (2%) Acne medication

ASK DOCTOR

Ask a physician
n If symptoms last for more than 7 days or clear up and recur within a few days.
n If the conditions do not improve.
n Before use on children under 2 years.
n Before use if you are allergic to any ingredients listed on this label.

DO NOT USE

n When using this product, skin irritation and dryness is more likely to occur if you use another topical acne medication at the same time. If irritation occurs, only use one topical acne medication at a time.
n Keep away from children
n Avoid contact with eyes
n May be harmful if swallowed or inhaled

CHILDREN

Keep away from children
Avoid contact with eyes
May be harmful if swallowed or inhaled

PURPOSE

Active Ingredient Purpose
Salicylic acid (2%) Acne medication
______________________________________
Uses
n Acne medication lotion. For the treatment of acne. Clears up most acne blemishes and allows skin to heal.

STOP USE

n When using this product, skin irritation and dryness is more likely to occur if you use another topical acne medication at the same time. If irritation occurs, only use one topical acne medication at a time.

WHEN USING

For external use only
Avoid contact with eyes
May be harmful if swallowed or inhaled
If symptoms last for more than 7 days or clear up and recur within a few days.
If the conditions do not improve.
Store at 40 to 120 degrees F.

WARNINGS

n For external use only
n When using this product, skin irritation and dryness is more likely to occur if you use another topical acne medication at the same time. If irritation occurs, only use one topical acne medication at a time.
n Keep away from children
n Avoid contact with eyes
n May be harmful if swallowed or inhaled

DOSAGE & ADMINISTRATION

Uses
n Acne medication lotion. For the treatment of acne. Clears up most acne blemishes and allows skin to heal.
______________________________________
Directions
n Clean the skin thoroughly before applying this product.
n Apply product sparingly to one or two small affected areas during the first 3 days. If no discomfort occurs, follow the directions stated below.
n Each morning, cover the entire affected area with a thin layer of this product.
n Apply this product by rubbing it in. If any liquid remains on the skin (after a 20-second rub-in), you have applied too much product.

USE

Uses
n Acne medication lotion. For the treatment of acne. Clears up most acne blemishes and allows skin to heal.
______________________________________
Directions
n Clean the skin thoroughly before applying this product.
n Apply product sparingly to one or two small affected areas during the first 3 days. If no discomfort occurs, follow the directions stated below.
n Each morning, cover the entire affected area with a thin layer of this product (ACNE22).
n Apply this product by rubbing it in. If any liquid remains on the skin (after a 20-second rub-in), you have applied too much product.

INACTIVE INGREDIENTS

Water, dimethyl sulfoxide, dipropylene glycol, ascorbic acid, sorbic acid, magnesium stearate, stearic acid.

Image of product